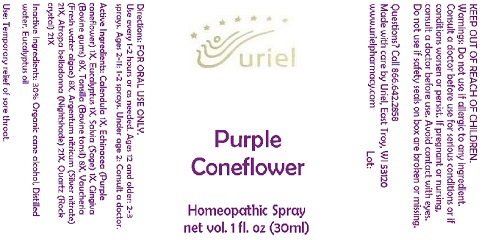 DRUG LABEL: Purple Coneflower
NDC: 48951-8318 | Form: SPRAY
Manufacturer: Uriel Pharmacy Inc
Category: homeopathic | Type: HUMAN OTC DRUG LABEL
Date: 20170724

ACTIVE INGREDIENTS: SAGE 1 [hp_X]/1 1; CALENDULA OFFICINALIS FLOWERING TOP 1 [hp_X]/1 1; ECHINACEA PALLIDA 1 [hp_X]/1 1; EUCALYPTUS GLOBULUS LEAF 1 [hp_X]/1 1; MERCURIC CYANIDE 8 [hp_X]/1 1; SILVER NITRATE 20 [hp_X]/1 1; ATROPA BELLADONNA 20 [hp_X]/1 1; SILICON DIOXIDE 20 [hp_X]/1 1
INACTIVE INGREDIENTS: ALCOHOL; WATER; EUCALYPTUS OIL

Purple Coneflower Spray - 1 oz.

Purpose

Uses: Temporary relieves symptoms of sore throat and mouth inflammation.

Dosage & Administration

Directions: Take up to every 1-2 hours as needed. Ages 12 and older: 2-3 sprays. Ages 2-11: 1-2 sprays. Under age 2: Ask a doctor.

OTC-Active Ingredient

Active Ingredients: Calendula 1X, Echinacea (Purple coneflower) 1X, Eucalyptus 1X, Salvia (Sage) 1X, Gingiva (Bovine gums) 8X, Tonsilla (Bovine tonsil) 8X, Vaucheria (Fresh water algae) 8X, Argentum nitricum (Silver nitrate) 21X, Atropa belladonna (Nightshade) 21X, Quartz (Rock crystal) 21X

Inactive Ingredient

Inactive Ingredients: Organic cane alcohol, Water, Eucalyptus oil, Gingiva, Tonsilla, Vaucheria.

Keep out of reach of children

Do not use if allergic to any ingredient. Do not use if safety seal is broken or missing.

Ask doctor section

Consult a doctor if symptoms worsen or persist.

Pregnancy or breast feeding section

If you are pregnant or nursing, consult a doctor before use.

Questions section

Questions? Uriel Pharmacy

866 642-2858 East Troy, WI 53120

www.urielpharmacy.com